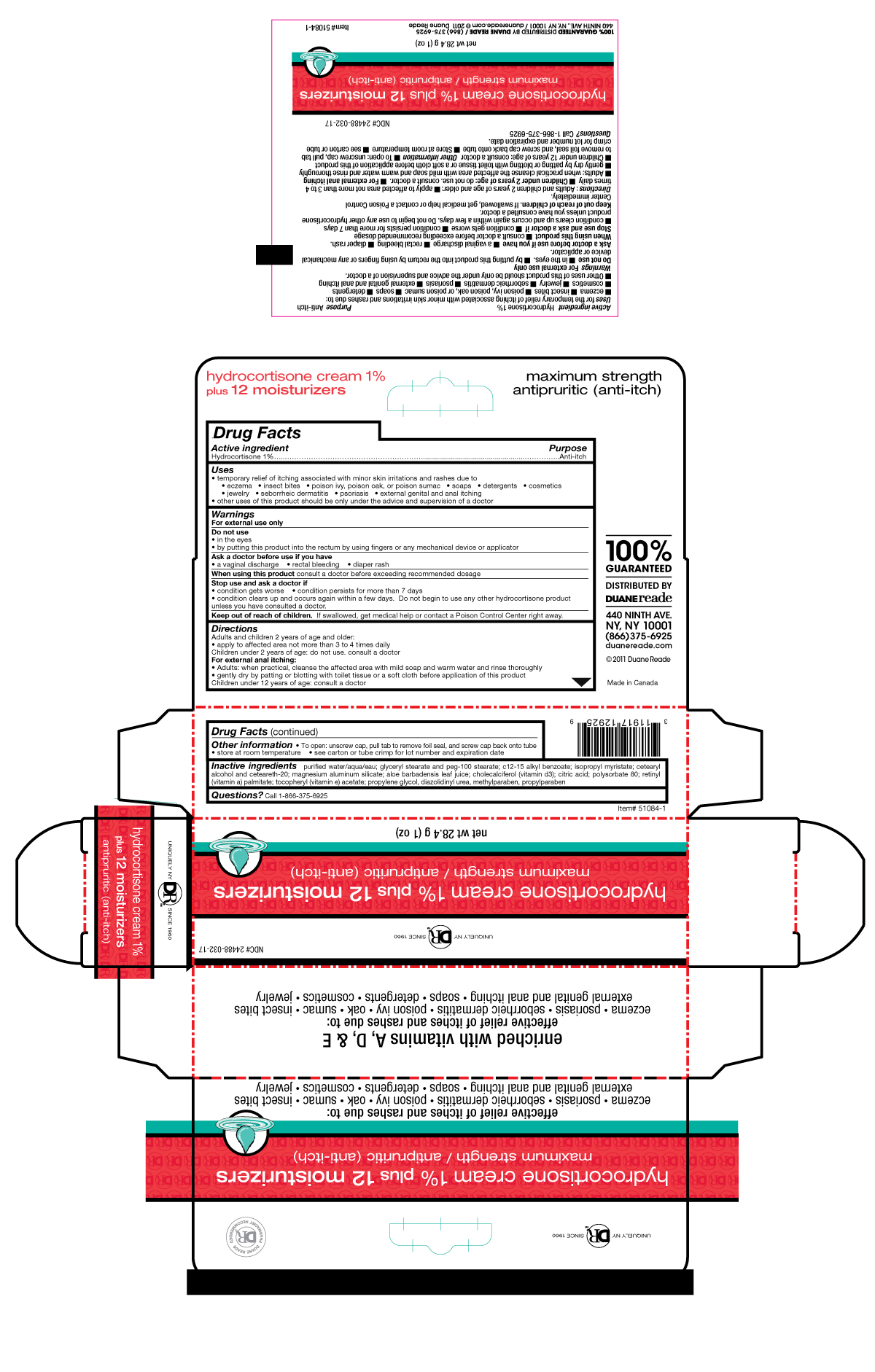 DRUG LABEL: Duane Reade
NDC: 24488-032 | Form: CREAM
Manufacturer: Duane Reade
Category: otc | Type: HUMAN OTC DRUG LABEL
Date: 20110328

ACTIVE INGREDIENTS: HYDROCORTISONE .284 g/287.4 g
INACTIVE INGREDIENTS: WATER; GLYCERYL MONOSTEARATE; PEG-100 STEARATE; ALKYL (C12-15) BENZOATE; ISOPROPYL MYRISTATE; CETOSTEARYL ALCOHOL; POLYOXYL 20 CETOSTEARYL ETHER; MAGNESIUM ALUMINUM SILICATE; ALOE VERA LEAF; CHOLECALCIFEROL; CITRIC ACID MONOHYDRATE; POLYSORBATE 80; VITAMIN A PALMITATE; PROPYLENE GLYCOL; DIAZOLIDINYL UREA; METHYLPARABEN; PROPYLPARABEN

Drug Facts

Active ingredient........................Purpose

Hydrocortison 1%........................Anti-itch

Uses

temporarily relief of itching associated with minor skin irritations and rashes due to

- eczema
- insect bites
- poison ivy, poison oak, and poison sumac
- soaps
- detergents
- cosmetics
- other uses of this product should be only under the advice and supervision of a doctor

Warnings

For external use only.

Do not use

- in the eyes
- by putting this product into the rectum by using fingers or any mechanical device or applicator.

Ask a doctor before use if you have

- vaginal discharge
- rectal bleeding
- diaper rash

When using this product

consult a doctor before exceeding the recommended dosage

Stop use and ask a doctor if

- condition gets worse
- condition persists for more than 7 days
- condition clears up and occurs again within a few days. Do not begin to use another hydrocortisone product unless you have consulted a doctor.

Keep out of reach of children.

If swallowed, get medical help or contact a Poison Control Center right away.

Directions

Adult and children 2 years of age and older:

- apply to the affected area no more than 3-4 times daily

children under 2 years: do not use. Consult a doctor.
For external anal itching:

- Adults: when practical, cleanse the affected area with mild soap and warm water and rinse thoroughly
- gently dry by patting or blotting with toilet tissue or a soft cloth before application of this product.

Children under 12 years of age: consult a doctor.

Other information

To open: unscrew cap, pull tab to remove foil seal and screw cap back onto tube.

- store at room temperature
- see carton or tube crimp for lot number and expiration date

Inactive ingredients

purified water/aqua/eau; glyceryl stearate and peg-100 stearate; c12-15 alkyl benzoate; isopropyl myristate; cetearyl alcohol and ceteareth-20; magnesium aluminium silicate; aloe barbadensis leaf juice; cholecalciferol (vitamin d3); citric acid; polysorbate 80; retinyl (vitamin a) palmitate; tocopheryl (vitamin e) acetate; propylene glycol; diazolidinyl urea; methylparaben; propylparaben

Questions?

Call 1-866-375-6925

PACKAGE LABEL

place holder text